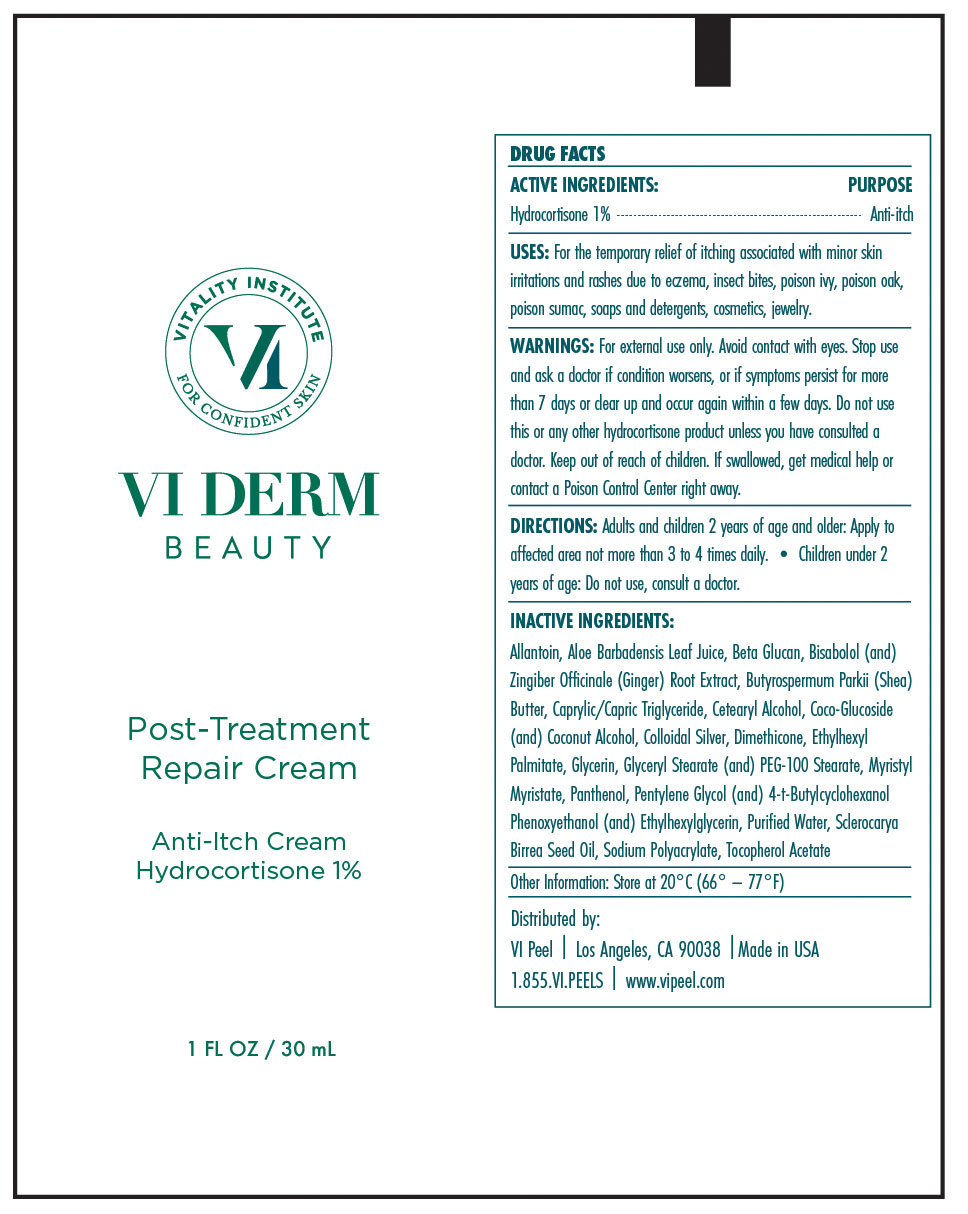 DRUG LABEL: Post-Treatment Repair Cream
NDC: 70484-007 | Form: CREAM
Manufacturer: Vi Medical Products Inc.
Category: otc | Type: HUMAN OTC DRUG LABEL
Date: 20250619

ACTIVE INGREDIENTS: HYDROCORTISONE 1 g/100 mL
INACTIVE INGREDIENTS: GINGER; SHEA BUTTER; COCO GLUCOSIDE; COCONUT ALCOHOL; DIMETHICONE; MYRISTYL MYRISTATE; PHENOXYETHANOL; SCLEROCARYA BIRREA SEED OIL; SODIUM POLYACRYLATE (2500000 MW); .ALPHA.-TOCOPHEROL ACETATE; ALLANTOIN; ALOE VERA LEAF; CETOSTEARYL ALCOHOL; SILVER; ETHYLHEXYL PALMITATE; GLYCERIN; GLYCERYL MONOSTEARATE; PEG-100 STEARATE; ETHYLHEXYLGLYCERIN; PANTHENOL; PENTYLENE GLYCOL; 4-TERT-BUTYLCYCLOHEXANOL; CURDLAN; LEVOMENOL; MEDIUM-CHAIN TRIGLYCERIDES; WATER

Post-Treatment Repair Cream

ACTIVE INGREDIENTS

Hydrocortisone 1% Purpose Anti-itch

USES

For the temporary relief of itching associated with minor skin irritations and rashes due to eczema, insect bites, poison ivy, poison oak, poison sumac, soaps and detergents, cosmetics, jewelry.

Keep out of reach of children. If swallowed, get medical help or contact a Poison Control Center right away.

INDICATIONS AND USAGE

Children under 2 years of age: Do not use, consult a doctor.

WARNINGS

For external use only. Avoid contact with eyes. Stop use and ask a doctor if condition worsens, or if symptoms persist for more than 7 days or clear up and occur again within a few days. Do not use this or any other hydrocortisone product unless you have consulted a doctor. Keep out of reach of children. If swallowed, get medical help or contact a Poison Control Center right away.

DIRECTIONS

Adults and children 2 years of age and older: Apply to affected area not more than 3 to 4 times daily. Children under 2 years of age: Do not use, consult a doctor.

INACTIVE INGREDIENTS

Allantoin, Aloe Barbadensis Leaf Juice, Beta GLucan, Bisabolol (and) Zingiber Officinale (Ginger) Root Extract, Butyrospermum Parkii (Shea) Butter, Caprylic/Capric Triglyceride, Cetearyl Alcohol, Coco-Glucoside (and) Coconut Alcohol, Colloidal Silver, Dimethicone, Ethylhexyl Palmitate, Glycerin, Glyceryl Stearate (and) PEG-100 Stearate, Myristyl Myristate, Panthenol, Pentylene Glycol (and) 4-t-Butylcyclohexanol, Phenoxyethanol (and) Ethylhexylglycerin, Purified Water, Sderocarya Birrea Seed Oil, Sodium Polyacrylate, Tocopherol Acetate

STORAGE AND HANDLING

Store at 20C (66 - 77F)

PACKAGE LABEL

VI DERM Beauty

Post-Treament Repair Cream

Anti-Itch Cream Hydrocortisone 1%

1 FL OZ / 30mL